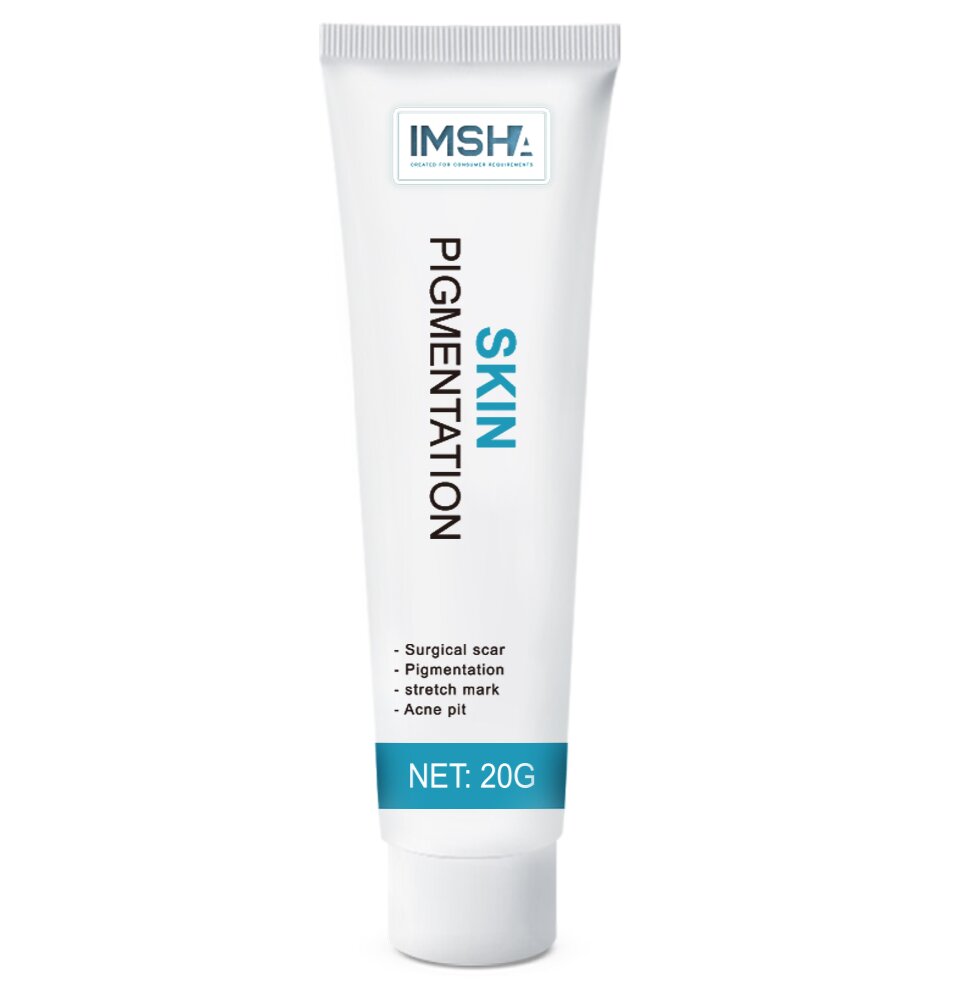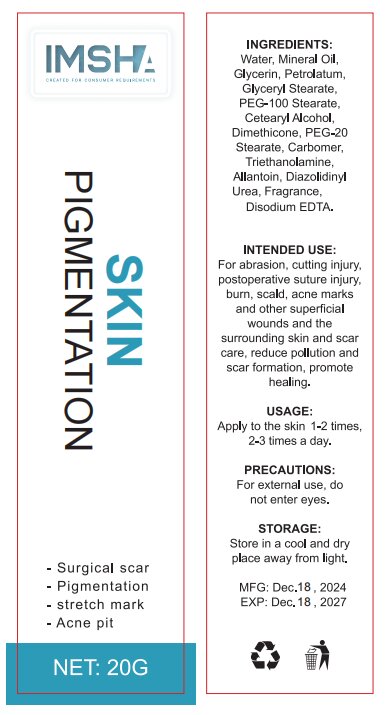 DRUG LABEL: SKIN PIGMENTATION
NDC: 84025-287 | Form: CREAM
Manufacturer: Guangzhou Yanxi Biotechnology Co., Ltd
Category: otc | Type: HUMAN OTC DRUG LABEL
Date: 20241219

ACTIVE INGREDIENTS: MINERAL OIL 5 mg/100 g; GLYCERIN 3 mg/100 g
INACTIVE INGREDIENTS: WATER

DOSAGE AND ADMINISTRATION

Apply to the skin 1-2 times, 2-3 times a day.

WARNINGS

Keep out of children

INACTIVE INGREDIENT

Aqua

INDICATIONS AND USAGE

for daily face care.

keep out of children

PURPOSE

Improve skin quality